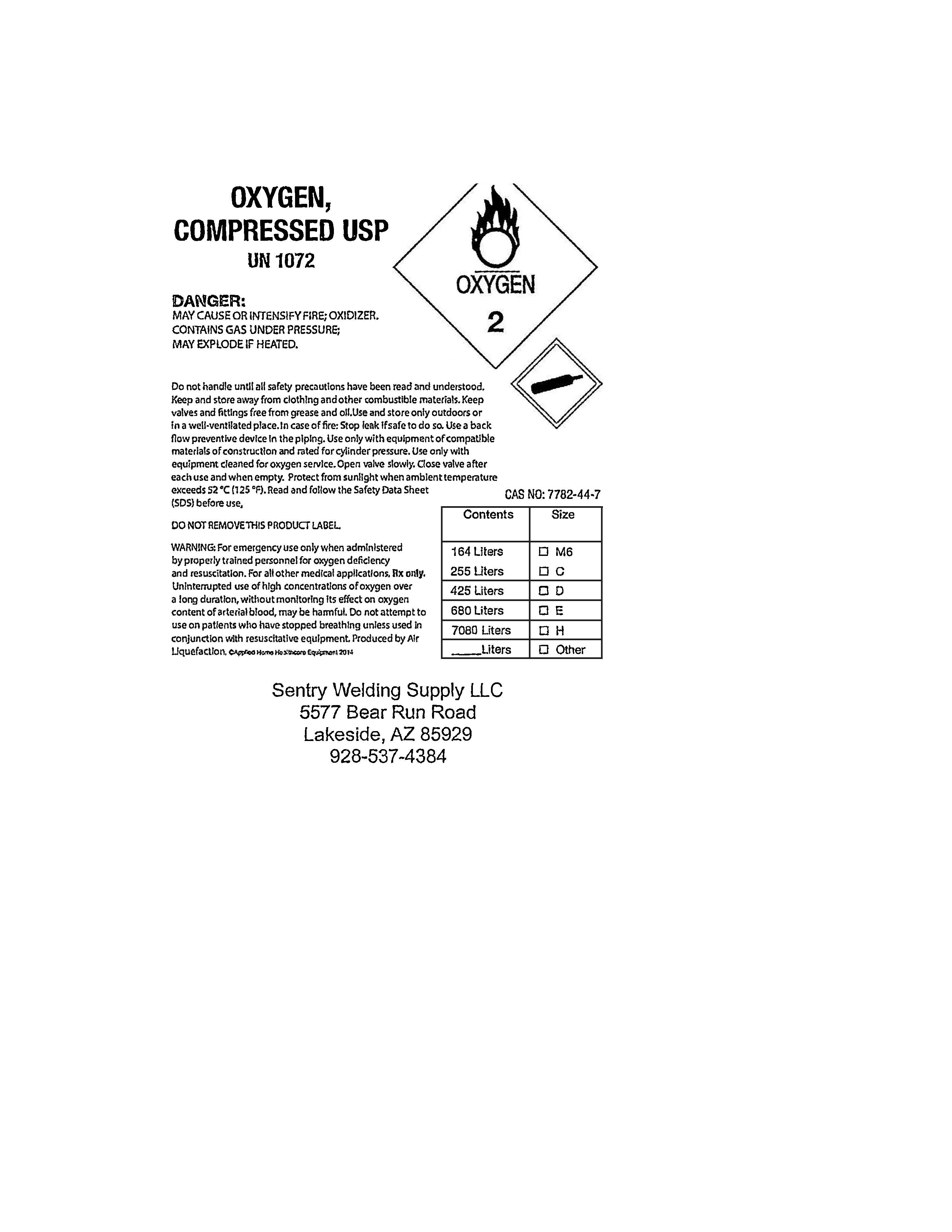 DRUG LABEL: Oxygen
NDC: 87133-463 | Form: GAS
Manufacturer: Sentry Welding Supply LLC
Category: prescription | Type: HUMAN PRESCRIPTION DRUG LABEL
Date: 20250924

ACTIVE INGREDIENTS: OXYGEN 992 mL/1 L

Oxygen Medical Gas

Medical Oxygen Label - Sentry Welding Supply LLC

Oxygen Label.jpg